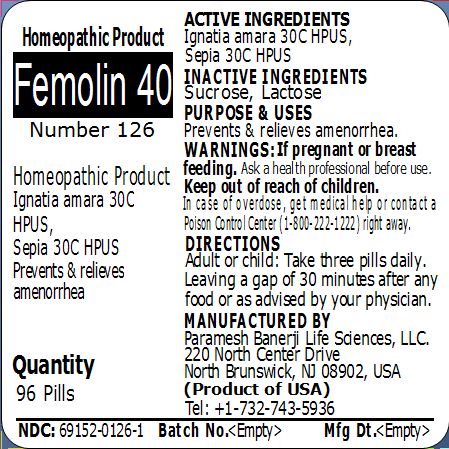 DRUG LABEL: Femolin 40 Number 126
NDC: 69152-0126 | Form: PELLET
Manufacturer: Paramesh Banerji Life Sciences LLC
Category: homeopathic | Type: HUMAN OTC DRUG LABEL
Date: 20150318

ACTIVE INGREDIENTS: STRYCHNOS IGNATII SEED 30 [hp_C]/1 1; SEPIA OFFICINALIS JUICE 30 [hp_C]/1 1
INACTIVE INGREDIENTS: SUCROSE; LACTOSE

Active Ingredients

Ignatia amara 30C HPUS, Sepia 30C HPUS

Inactive Ingredients

Sucrose, Lactose

Purpose

Prevents & relieves amenorrhea

Uses

Prevents & relieves amenorrhea

Warnings

If pregnant or breast feeding ask a health professional before use.

Keep out of reach of children. In case of overdose, get medical help or contact a Poison Control Center (1-800-222-1222) right away.

Direction

Adult or child: Take three pills daily. Leaving a gap of 30 minutes after any food or as advised by your physician.

Manufactured by

Paramesh Banerji Life Sciences, LLC

220 North Center Drive

North Brunswick, NJ 08902, USA

Product of USA

Tel: +1-732-743-5936

Principal Display Panel

Homeopathic Product

Femolin 40

Number 126

Homeopathic Product

Ignatia amara 30C HPUS, Sepia 30C HPUS

Prevents & relieves amenorrhea

Quantity

96 Pills